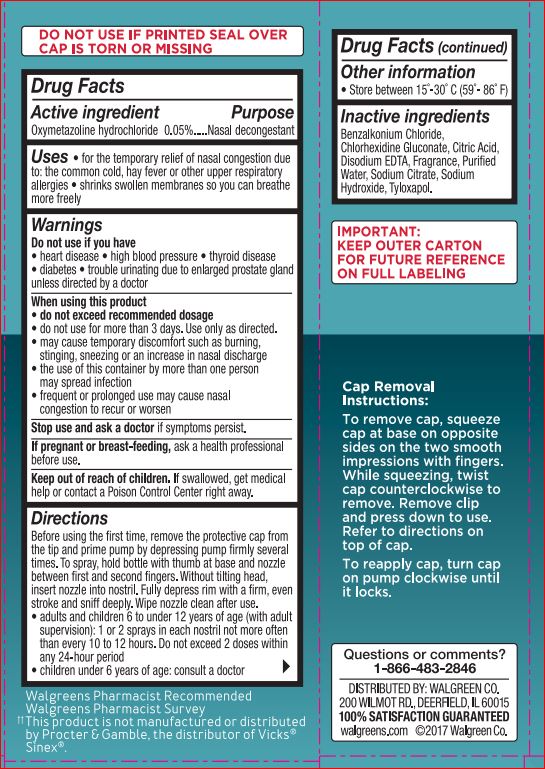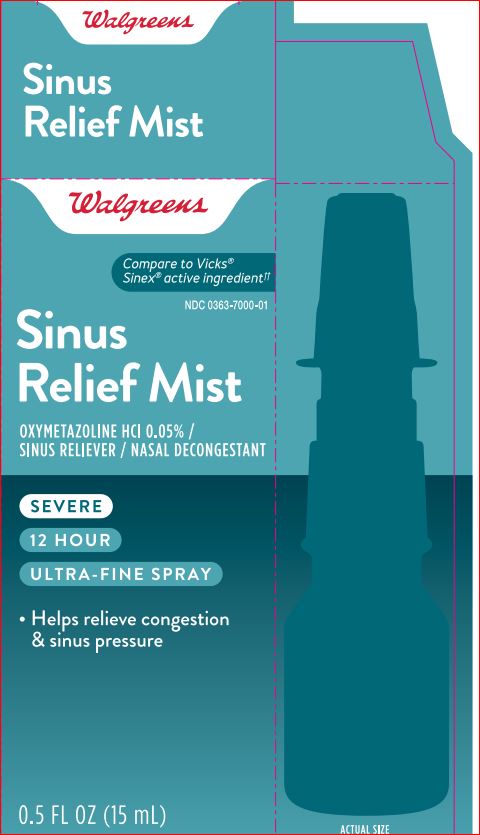 DRUG LABEL: Nasal Mist
NDC: 0363-7000 | Form: LIQUID
Manufacturer: Walgreens
Category: otc | Type: HUMAN OTC DRUG LABEL
Date: 20180614

ACTIVE INGREDIENTS: Oxymetazoline Hydrochloride 0.05 g/100 mL
INACTIVE INGREDIENTS: Benzalkonium Chloride; Water; Chlorhexidine Gluconate; CITRIC ACID MONOHYDRATE; EDETATE DISODIUM; Sodium Citrate; Sodium Hydroxide; Tyloxapol

Drug Facts

Active ingredient Purpose

Oxymetazoline Hydrochloride 0.05% Nasal decongestant

Uses

• for the temporary relief of nasal congestion due to
the common cold, hay fever or other upper respiratory
allergies

• shrinks swollen membranes so you can breathe
more freely

Warnings

Do not use this product if you have heart disease • high
blood pressure • thyroid disease
• diabetes • or difficulty in urination due to enlargement of
the prostate gland

When using this product

•do not exceed recommended dosage • do not use for more than 3 days. Use only as directed. • may cause temporary discomfort such as burning, stinging, sneezing or an increase in nasal discharge • the use of this container by more than one person may spread infection • frequent or prolonged use may cause nasal congestion to recur or worsen

Keep out of reach of children. If product is swallowed, get medical help or contact a PoisonControl Center right away

Directions

Before using the first time, remove the protective cap from the tip and prime pump by depressing pump firmly several times.
To spray, hold bottle with thumb at base and nozzle between first and second fingers. Without tilting head, insert nozzle into nostril. Fully depress rim with a firm, even stroke and sniff deeply. Wipe nozzle clean after use. • adults and children 6 to under1 2 years of age (with adult supervision): 2 or 3 sprays in each nostril not more often than every 1 0 to 1 2 hours. Do not exceed 2 doses within any 24-hour period • children under 6 years of age: consult a doctor

Inactive ingredients

Benzalkonium Chloride
Chlorhexidine Gluconate
Citric Acid
Disodium EDTA
Fragrance
Purified Water
Sodium Citrate
Sodium Hydroxide
Tyloxapol